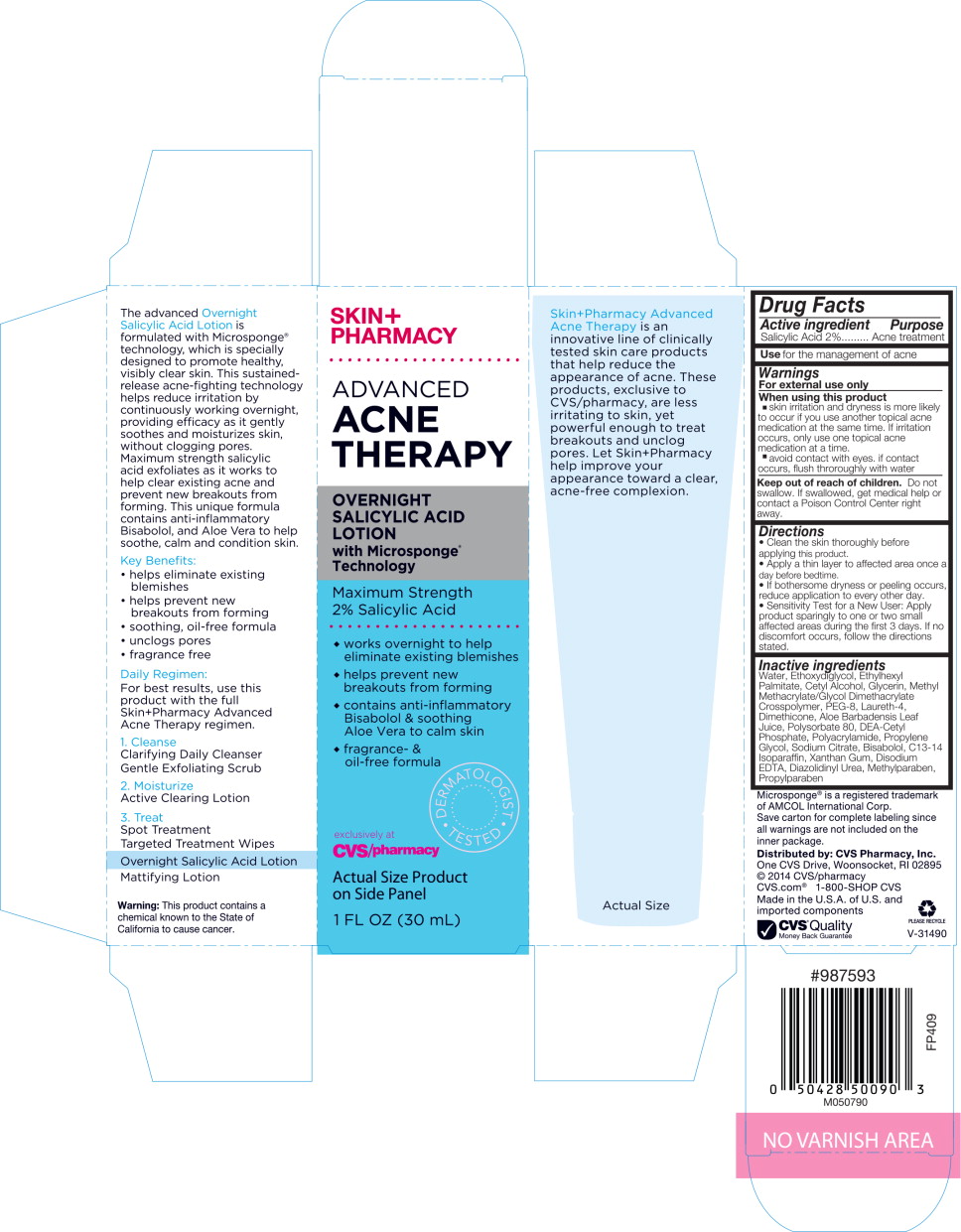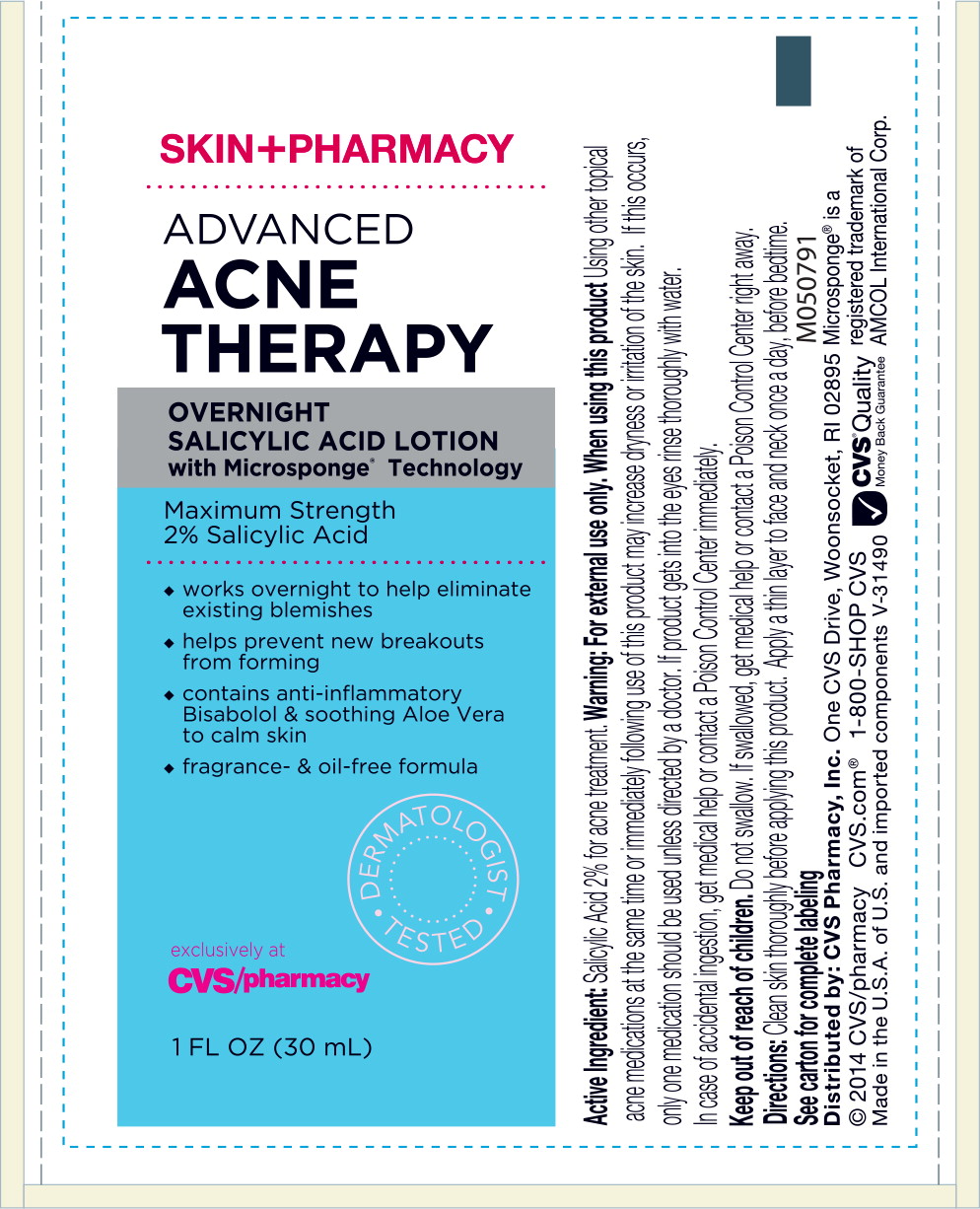 DRUG LABEL: SKINPHARMACY ADVANCED ACNE THERAPY OVERNIGHT SALICYLIC ACID
NDC: 69842-066 | Form: LIQUID
Manufacturer: CVS Health
Category: otc | Type: HUMAN OTC DRUG LABEL
Date: 20170314

ACTIVE INGREDIENTS: salicylic acid 20 mg/1 mL
INACTIVE INGREDIENTS: WATER; DIETHYLENE GLYCOL MONOETHYL ETHER; ETHYLHEXYL PALMITATE; CETYL ALCOHOL; METHYL METHACRYLATE/GLYCOL DIMETHACRYLATE CROSSPOLYMER; POLYETHYLENE GLYCOL 400; LAURETH-4; DIMETHICONE; ALOE VERA LEAF; POLYSORBATE 80; DIETHANOLAMINE CETYL PHOSPHATE; POLYACRYLAMIDE (1500 MW); 1,2-PROPANEDIOL, 1-BENZOATE; SODIUM CITRATE, UNSPECIFIED FORM; LEVOMENOL; C13-14 ISOPARAFFIN; XANTHAN GUM; EDETATE DISODIUM; DIAZOLIDINYL UREA; METHYLPARABEN; PROPYLPARABEN

Drug Facts

Active Ingredient

Salicylic Acid 2%

Purpose

Acne treatment

Use

for the management of acne

Warnings

For external use only

When using this product

- skin irritation and dryness is more likely to occur if you use another topical acne medication at the same time. If irritation occurs, only use one topical acne medication at a time.
- avoid contact with eyes. If contact occurs, flush thoroughly with water

Keep out of reach of children. Do not swallow. If swallowed, get medical help or contact a Poison Control Center right away.

Directions

- Clean the skin thoroughly before applying this product.
- Apply a thin layer to affected area once a day before bedtime.
- If bothersome dryness or peeling occurs, reduce application to every other day.
- Sensitivity Test for a New User: Apply product sparingly to one or two small affected areas during the first 3 days. If no discomfort occurs, follow the directions stated.

Inactive ingredients

Water, Ethoxydiglycol, Ethylhexyl Palmitate, Cetyl Alcohol, Glycerin, Methyl Methacrylate/Glycol Dimethacrylate Crosspolymer, PEG-8, Laureth-4, Dimethicone, Aloe Barbadensis Leaf Juice, Polysorbate 80, DEA-Cetyl Phosphate, Polyacrylamide, Propylene Glycol, Sodium Citrate, Bisabolol, C13-14 Isoparaffin, Xanthan Gum, Disodium EDTA, Diazolidinyl Urea, Methylparaben, Propylparaben

Microsponge® is a registered trademark of AMCOL International Corp.

Save carton for complete labeling since all warnings are not included on the inner package.

Distributed by: CVS Pharmacy, Inc.

One CVS Drive, Woonsocket, RI 02895

© 2014 CVS/pharmacy

CVS.com® 1-800-SHOP CVS

Made in the U.S.A. of U.S. and foreign components

CVS® Quality

Money Back Guarantee

V-13649

PLEASE RECYCLE

V-31490

#987593

FP409

M050790

Principal Display Panel - Carbon Label

SKIN+
PHARMACY

ADVANCED
ACNE
THERAPY

OVERNIGHT
SALICYLIC
ACID
LOTION
with Microsponge®
Technology

Maximum Strength 2% Salicylic Acid

- works overnight to help eliminate existing blemishes
- helps prevent new breakouts from forming
- contains anti-inflammatory Bisabolol & soothing Ale Vera to calm skin
- fragrance- & oil-free formula

DERMATOLOGIST TESTED

exclusively at
CVS/pharmacy

Actual Size Product
on Side Panel

1 FL OZ (30 mL)

Principal Display Panel - Tube Label

SKIN+PHARMACY

ADVANCED
ACNE
THERAPY

OVERNIGHT
SALICYLIC ACID LOTION
with Microsponge® Technology

Maximum Strength
2% Salicylic Acid

- works overnight to help eliminate existing blemishes
- helps prevent new breakouts from forming
- contains anti-inflammatory Bisabolol & soothing Aloe Vera to calm skin
- fragrance- & oil-free formula

DERMATOLOGIST TESTED

exclusively at
CVS/pharmacy

1 FL OZ (30 mL)